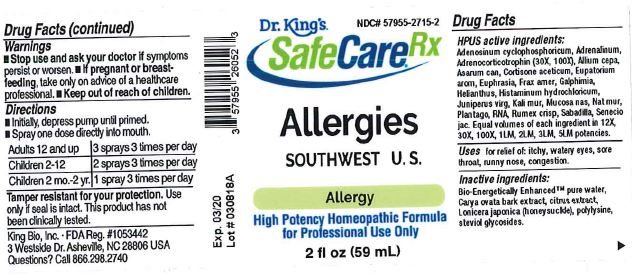 DRUG LABEL: Allergies Southwest U.S.
NDC: 57955-2715 | Form: LIQUID
Manufacturer: King Bio Inc.
Category: homeopathic | Type: HUMAN OTC DRUG LABEL
Date: 20180626

ACTIVE INGREDIENTS: ADENOSINE CYCLIC PHOSPHATE 12 [hp_X]/59 mL; EPINEPHRINE 12 [hp_X]/59 mL; CORTICOTROPIN 30 [hp_X]/59 mL; ONION 12 [hp_X]/59 mL; ASARUM CANADENSE ROOT 12 [hp_X]/59 mL; CORTISONE ACETATE 12 [hp_X]/59 mL; AGERATINA AROMATICA ROOT 12 [hp_X]/59 mL; EUPHRASIA STRICTA 12 [hp_X]/59 mL; FRAXINUS AMERICANA BARK 12 [hp_X]/59 mL; GALPHIMIA GLAUCA FLOWERING TOP 12 [hp_X]/59 mL; HELIANTHUS ANNUUS FLOWERING TOP 12 [hp_X]/59 mL; HISTAMINE DIHYDROCHLORIDE 12 [hp_X]/59 mL; JUNIPERUS VIRGINIANA TWIG 12 [hp_X]/59 mL; POTASSIUM CHLORIDE 12 [hp_X]/59 mL; SUS SCROFA NASAL MUCOSA 12 [hp_X]/59 mL; SODIUM CHLORIDE 12 [hp_X]/59 mL; PLANTAGO MAJOR 12 [hp_X]/59 mL; SACCHAROMYCES CEREVISIAE RNA 12 [hp_X]/59 mL; RUMEX CRISPUS ROOT 12 [hp_X]/59 mL; SCHOENOCAULON OFFICINALE SEED 12 [hp_X]/59 mL; JACOBAEA VULGARIS 12 [hp_X]/59 mL
INACTIVE INGREDIENTS: WATER; CARYA OVATA BARK; CITRUS BIOFLAVONOIDS; LONICERA JAPONICA FLOWER; POLYEPSILON-LYSINE (4000 MW); REBAUDIOSIDE A

Allergies
Southwest U.S.

Drug Facts

____________________________________________________________________________________________________________________

HPUS active ingredients: Adenosinum cyclophosphoricum, Adrenalinum, Adrenocorticotrophin, Allium cepa, Asarum can, Cortisone aceticum, Eupatorium arom, Euphrasia, Frax amer, Galphimia, Helianthus, Histaminum hydrochloricum, Juniperus virg, Kali mur, Mucosa nas, Nat mur, Plantago, RNA, Rumex crisp, Sabadilla, Senecio jac

Equal volumes of each ingredient in 12X, 30X, 100X, 1LM, 2LM, 3LM, 5LM potencies.

INDICATIONS AND USAGE

Uses for relief of: itchy, watery eyes, sore throat, runny nose, congestion.

INACTIVE INGREDIENT

Inactive ingredients: Bio-Energetically Enhanced pure water, Carya ovata bark extract, citrus extract, Lonicera japonica (honeysuckle), polylysine, steviol glycosides.

Warnings

- Stop use and ask your doctor if symptoms persist or worsen.
- If pregnant or breast-feeding, take only on advice of a healthcare professional.

- Keep out of reach of children.

Directions:

- Initially, depress pump until primed.
- Spray one dose directly into mouth.
- Adults 12 and up: 3 sprays 3 times per day.
- Children 2-12: 2 sprays 3 times per day.
- Children 2 mo.-2yr: 1 spray 3 times per day.

OTHER SAFETY INFORMATION

Tamper resistant for your protection. Use only if safety seal is intact. This product has not been clinically tested.

PURPOSE

Uses for temporary relief of symptoms:

- itchy, watery eyes
- sore throat
- runny nose
- congestion